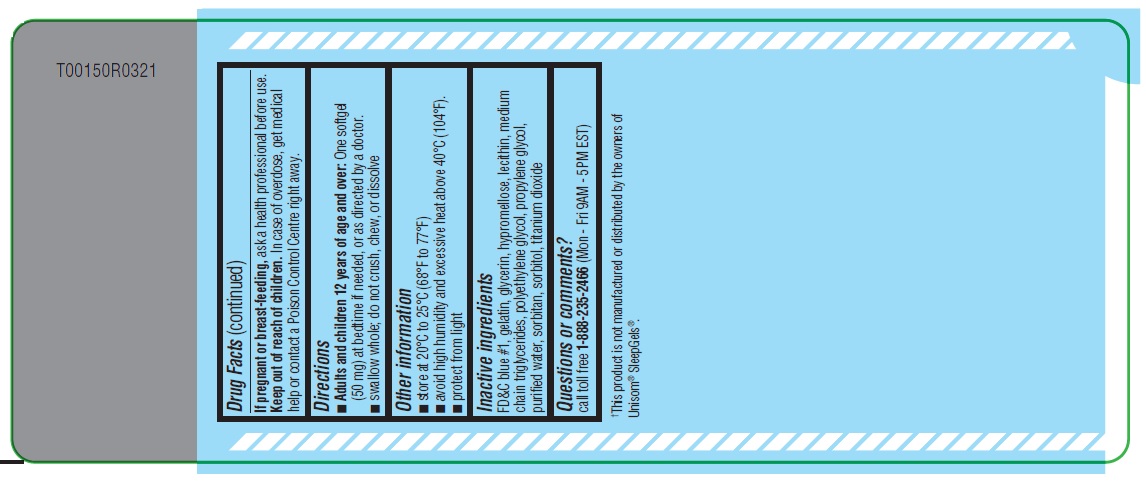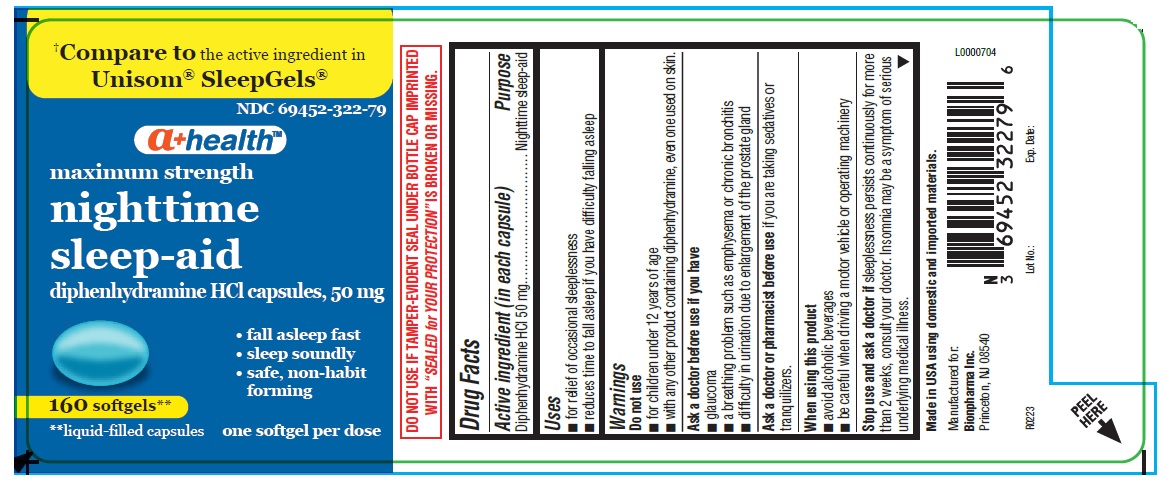 DRUG LABEL: nighttime sleep-aid
NDC: 69452-322 | Form: CAPSULE, LIQUID FILLED
Manufacturer: Bionpharma Inc.
Category: otc | Type: HUMAN OTC DRUG LABEL
Date: 20231226

ACTIVE INGREDIENTS: DIPHENHYDRAMINE HYDROCHLORIDE 50 mg/1 1
INACTIVE INGREDIENTS: GLYCERIN; GELATIN; LECITHIN, SOYBEAN; WATER; SORBITAN; MEDIUM-CHAIN TRIGLYCERIDES; TITANIUM DIOXIDE; POLYETHYLENE GLYCOL, UNSPECIFIED; FD&C BLUE NO. 1; HYPROMELLOSE, UNSPECIFIED

Drug Facts

Active ingredient (in each capsule)

Diphenhydramine HCl 50 mg

Purpose

Nighttime sleep-aid

Uses

■ for relief of occasional sleeplessness
■ reduces time to fall asleep if you have difficulty falling asleep

Warnings

Do not use

■ for children under 12 years of age
■ with any other product containing diphenhydramine, even one used on skin.

Ask a doctor before use if you have

■ glaucoma
■ a breathing problem such as emphysema or chronic bronchitis
■ difficulty in urination due to enlargement of the prostate gland

Ask a doctor or pharmacist before use

if you are taking sedatives or tranquilizers.

When using this product

■ avoid alcoholic beverages
■ be careful when driving a motor vehicle or operating machinery

Stop use and ask a doctor if

sleeplessness persists continuously for more than 2 weeks, consult your doctor. Insomnia may be a symptom of serious underlying medical illness.

If pregnant or breast-feeding,

ask a health professional before use.

Keep out of reach of children.

In case of overdose, get medical help or contact a Poison Control Centre right away.

Directions

■ Adults and children 12 years of age and over: One softgel (50 mg) at bedtime if needed, or as directed by a doctor.
■ swallow whole; do not crush, chew, or dissolve

Other information

■ store at 20°C to 25°C (68°F to 77°F)
■ avoid high humidity and excessive heat above 40°C (104°F).
■ protect from light

Inactive ingredients

FD&C blue #1, gelatin, glycerin, hypromellose, lecithin, medium chain triglycerides, polyethylene glycol, propylene glycol, purified water, sorbitan, sorbitol, titanium dioxide

Questions or comments?

call toll free 1-888-235-2466 (Mon - Fri 9AM - 5PM EST)

DO NOT USE IF TAMPER-EVIDENT SEAL UNDER BOTTLE CAP IMPRINTED WITH “ SEALED for YOUR PROTECTION” IS BROKEN OR MISSING.

†This product is not manufactured or distributed by the owners of Unisom®SleepGels®.

Made in USA using domestic and imported materials.

Manufactured for:
Bionpharma Inc.
Princeton, NJ 08540

R0223 Lot No.: Exp. Date

L0000704

160's count Label

†Compare to the active ingredient in Unisom®SleepGels®

NDC 69452-322-79

a+health

maximum strength

nighttime
sleep-aid

diphenhydramine HCl capsules, 50 mg

• fall asleep fast
• sleep soundly
• safe, non-habit forming

160 softgels**

**liquid-filled capsules

one softgel per dose